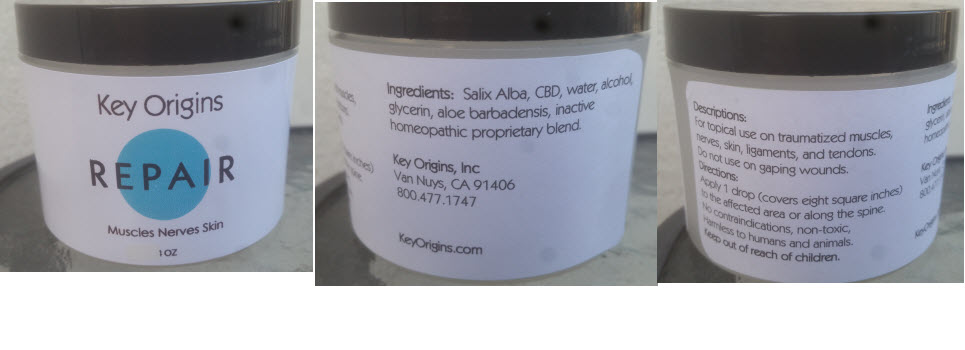 DRUG LABEL: Repair
NDC: 72186-001 | Form: GEL
Manufacturer: Key Origins, Inc.
Category: homeopathic | Type: HUMAN OTC DRUG LABEL
Date: 20181228

ACTIVE INGREDIENTS: Salix Alba Bark 6 [hp_X]/1 mL; Hemp 0.0492 mg/1 mL
INACTIVE INGREDIENTS: Water; Alcohol; Aloe Vera Leaf; Glycerin

Repair

Ingredients

INACTIVE INGREDIENT

Salix Alba, CBD, water, alcohol, glycerin, aloe barbadensis, inactive homeopathic proprietary blend.

Directions

Apply 1 drop (covers eight square inches) to the affected area or along the spine.

Descriptions

PURPOSE

For topical use on traumatized muscles, nerves, skin and ligaments and tendons. Do not use on gaping wounds.

No contraindications, nontoxic, harmless to humans and animals.

WARNINGS

Keep out of reach of children.

PRINCIPAL DISPLAY PANEL - 1 OZ Jar

Key Origins

REPAIR

Muscles Nerves Skin

1 OZ